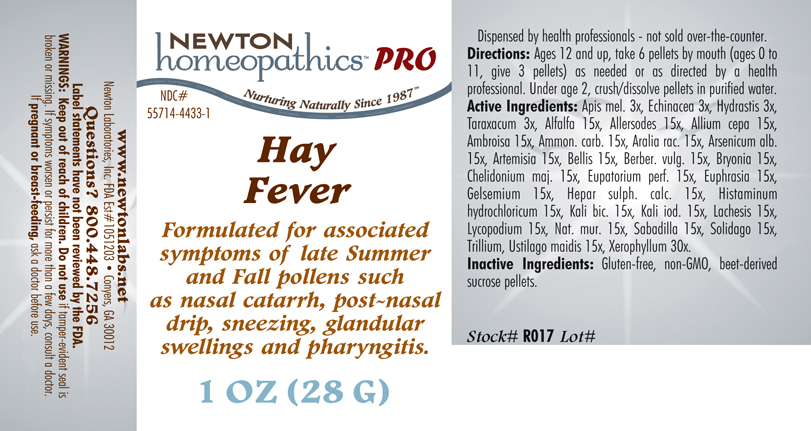 DRUG LABEL: Hay Fever 
NDC: 55714-4433 | Form: PELLET
Manufacturer: Newton Laboratories, Inc.
Category: homeopathic | Type: HUMAN PRESCRIPTION DRUG LABEL
Date: 20110601

ACTIVE INGREDIENTS: Xerophyllum Asphodeloides 30 [hp_X]/1 g; Alfalfa 15 [hp_X]/1 g; Avena Sativa Pollen 15 [hp_X]/1 g; Cynosurus Cristatus Pollen 15 [hp_X]/1 g; Echinochloa Crus-galli Pollen 15 [hp_X]/1 g; Poa Pratensis Pollen 15 [hp_X]/1 g; Anthoxanthum Odoratum Pollen 15 [hp_X]/1 g; Agrostis Gigantea Pollen 15 [hp_X]/1 g; Bromus Secalinus Pollen 15 [hp_X]/1 g; Alopecurus Pratensis Pollen 15 [hp_X]/1 g; Phleum Pratense Pollen 15 [hp_X]/1 g; Festuca Pratensis Pollen 15 [hp_X]/1 g; Holcus Lanatus Pollen 15 [hp_X]/1 g; Lolium Perenne Pollen 15 [hp_X]/1 g; Fagus Sylvatica Pollen 15 [hp_X]/1 g; Betula Pendula Pollen 15 [hp_X]/1 g; Quercus Alba Pollen 15 [hp_X]/1 g; Fraxinus Excelsior Pollen 15 [hp_X]/1 g; Corylus Americana Pollen 15 [hp_X]/1 g; Populus Nigra Pollen 15 [hp_X]/1 g; Platanus Orientalis Pollen 15 [hp_X]/1 g; Ulmus Glabra Pollen 15 [hp_X]/1 g; Salix Alba Pollen 15 [hp_X]/1 g; Narcissus Pseudonarcissus 15 [hp_X]/1 g; Rosa Canina Flower 15 [hp_X]/1 g; Lilium Candidum Flower 15 [hp_X]/1 g; Primula Vulgaris 15 [hp_X]/1 g; Dianthus Caryophyllus Flower 15 [hp_X]/1 g; Ulex Europaeus Flower 15 [hp_X]/1 g; Cytisus Scoparius Pollen 15 [hp_X]/1 g; Calluna Vulgaris Pollen 15 [hp_X]/1 g; Crataegus Monogyna Pollen 15 [hp_X]/1 g; Aconitum Napellus 15 [hp_X]/1 g; Arundo Pliniana Root 15 [hp_X]/1 g; Dysphania Ambrosioides 15 [hp_X]/1 g; Helianthemum Canadense 15 [hp_X]/1 g; Drosera Rotundifolia 15 [hp_X]/1 g; Solanum Dulcamara Top 15 [hp_X]/1 g; Ledum Palustre Twig 15 [hp_X]/1 g; Onosmodium Virginianum Whole 15 [hp_X]/1 g; Populus Tremuloides Leaf 15 [hp_X]/1 g; Populus Tremuloides Bark 15 [hp_X]/1 g; Pulsatilla Vulgaris 15 [hp_X]/1 g; Sanguinaria Canadensis Root 15 [hp_X]/1 g; Datura Stramonium 15 [hp_X]/1 g; Elymus Repens Root 15 [hp_X]/1 g; Urtica Urens 15 [hp_X]/1 g; Wyethia Helenioides Root 15 [hp_X]/1 g; Onion 15 [hp_X]/1 g; Ambrosia Artemisiifolia 15 [hp_X]/1 g; Ammonium Carbonate 15 [hp_X]/1 g; Aralia Racemosa Root 15 [hp_X]/1 g; Arsenic Trioxide 15 [hp_X]/1 g; Artemisia Vulgaris Root 15 [hp_X]/1 g; Bellis Perennis 15 [hp_X]/1 g; Berberis Vulgaris Root Bark 15 [hp_X]/1 g; Bryonia Alba Root 15 [hp_X]/1 g; Chelidonium Majus 15 [hp_X]/1 g; Eupatorium Perfoliatum Flowering Top 15 [hp_X]/1 g; Euphrasia Stricta 15 [hp_X]/1 g; Gelsemium Sempervirens Root 15 [hp_X]/1 g; Calcium Sulfide 15 [hp_X]/1 g; Histamine Dihydrochloride 15 [hp_X]/1 g; Potassium Dichromate 15 [hp_X]/1 g; Potassium Iodide 15 [hp_X]/1 g; Lachesis Muta Venom 15 [hp_X]/1 g; Lycopodium Clavatum Spore 15 [hp_X]/1 g; Sodium Chloride 15 [hp_X]/1 g; Schoenocaulon Officinale Seed 15 [hp_X]/1 g; Solidago Virgaurea Flowering Top 15 [hp_X]/1 g; Trillium Erectum Root 15 [hp_X]/1 g; Ustilago Maydis 15 [hp_X]/1 g; Apis Mellifera 3 [hp_X]/1 g; Echinacea, Unspecified 3 [hp_X]/1 g; Goldenseal 3 [hp_X]/1 g; Taraxacum Officinale 3 [hp_X]/1 g
INACTIVE INGREDIENTS: Sucrose

Hay Fever

INDICATIONS & USAGE SECTION

Formulated for associated symptoms of late Summer and Fall pollens such nasal catarrh, post~nasal drip, sneezing, glandular swellings and pharyngitis.

DOSAGE & ADMINISTRATION SECTION

Directions: Ages 12 and up, take 6 pellets by mouth (ages 0 to 11, give 3 pellets) as needed or as directed by a health professional. Under age 2, crush/dissolve pellets in purified water.

OTC - ACTIVE INGREDIENT SECTION

Xerophyllum 30x, Alfalfa 15x, Allersodes 15x, Allium cepa 15x, Ambrosia 15x, Ammon. carb. 15x, Aralia rac. 15x, Arsenicum alb. 15x, Artemisia 15x, Bellis 15x, Berber. vulg. 15x, Bryonia 15x , Chelidonium maj. 15x, Eupatorium perf. 15x, Euphrasia 15x, Gelsemium 15x, Hepar sulph. calc. 15x, Histaminum hydrochloricum 15x, Kali bic. 15x, Kali iod. 15x, Lachesis 15x, Lycopodium 15x, Nat.mur. 15x, Sabadilla 15x, Solidago 15x, Trillium 15x, Ustilago maidis 15x, Apis mel. 3x, Echinacea 3x, Hydrastis 3x, Taraxacum 3x.

OTC - PURPOSE SECTION

Formulated for associated symptoms of late Summer and Fall pollens such as nasal catarrh, post~nasal drip, sneezing, glandular swellings and pharyngitis.

INACTIVE INGREDIENT SECTION

Inactive Ingredients: Gluten-free, non-GMO, beet-derived sucrose pellets.

QUESTIONS SECTION

www.newtonlabs.net Newton Laboratories, Inc. FDA Est # 1051203 - Conyers, GA 30012
Questions? 1.800.448.7256

WARNINGS SECTION

Warning: Keep out of reach of children. Do not use if tamper-evident seal is broken or missing. If symptoms worsen or persist for more than a few days, consult a doctor. If pregnant or breast-feeding, ask a doctor before use.

OTC - PREGNANCY OR BREAST FEEDING SECTION

If pregnant or breast-feeding, ask a doctor before use.

OTC - KEEP OUT OF REACH OF CHILDREN SECTION

Keep out of reach of children.